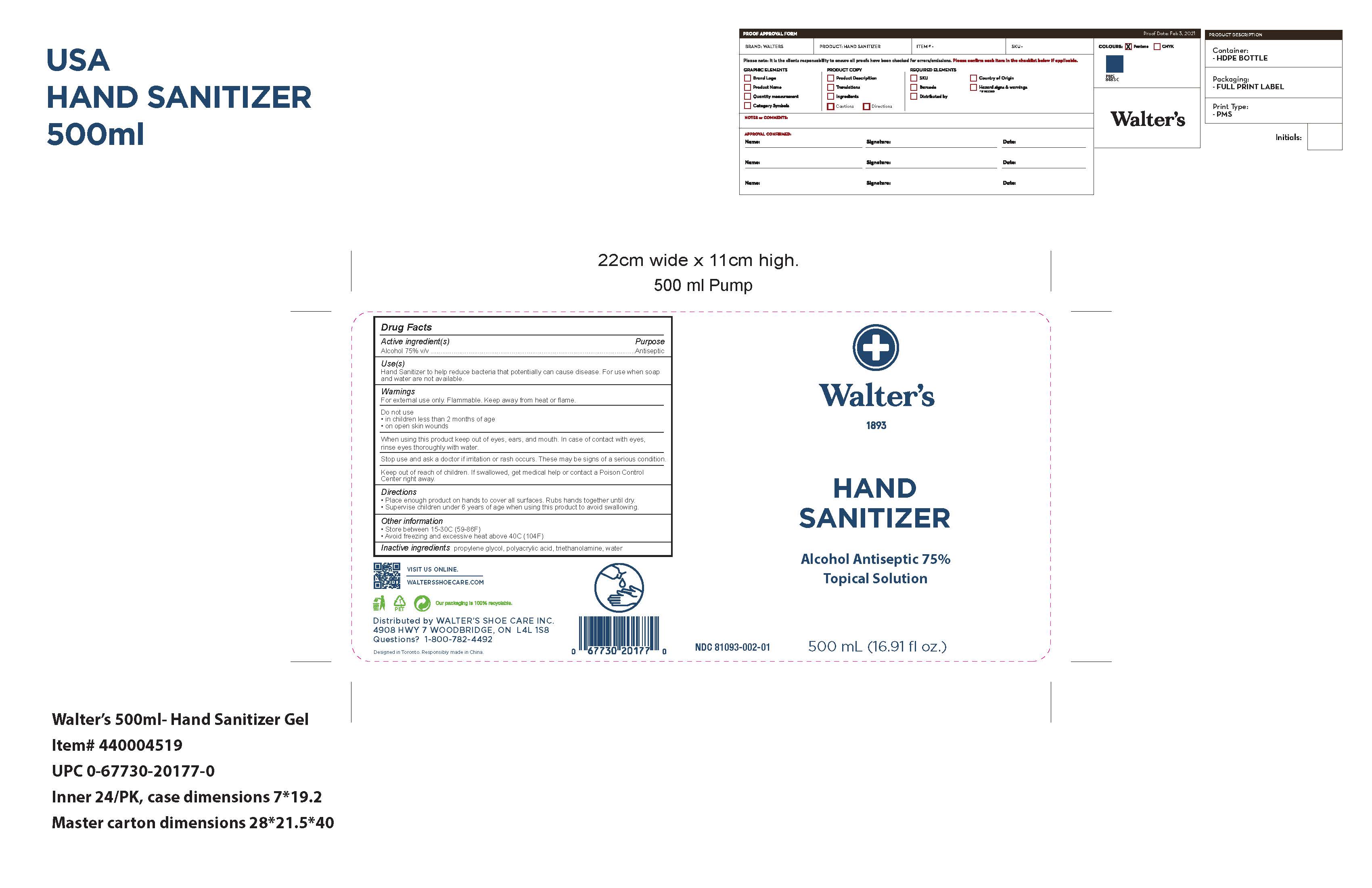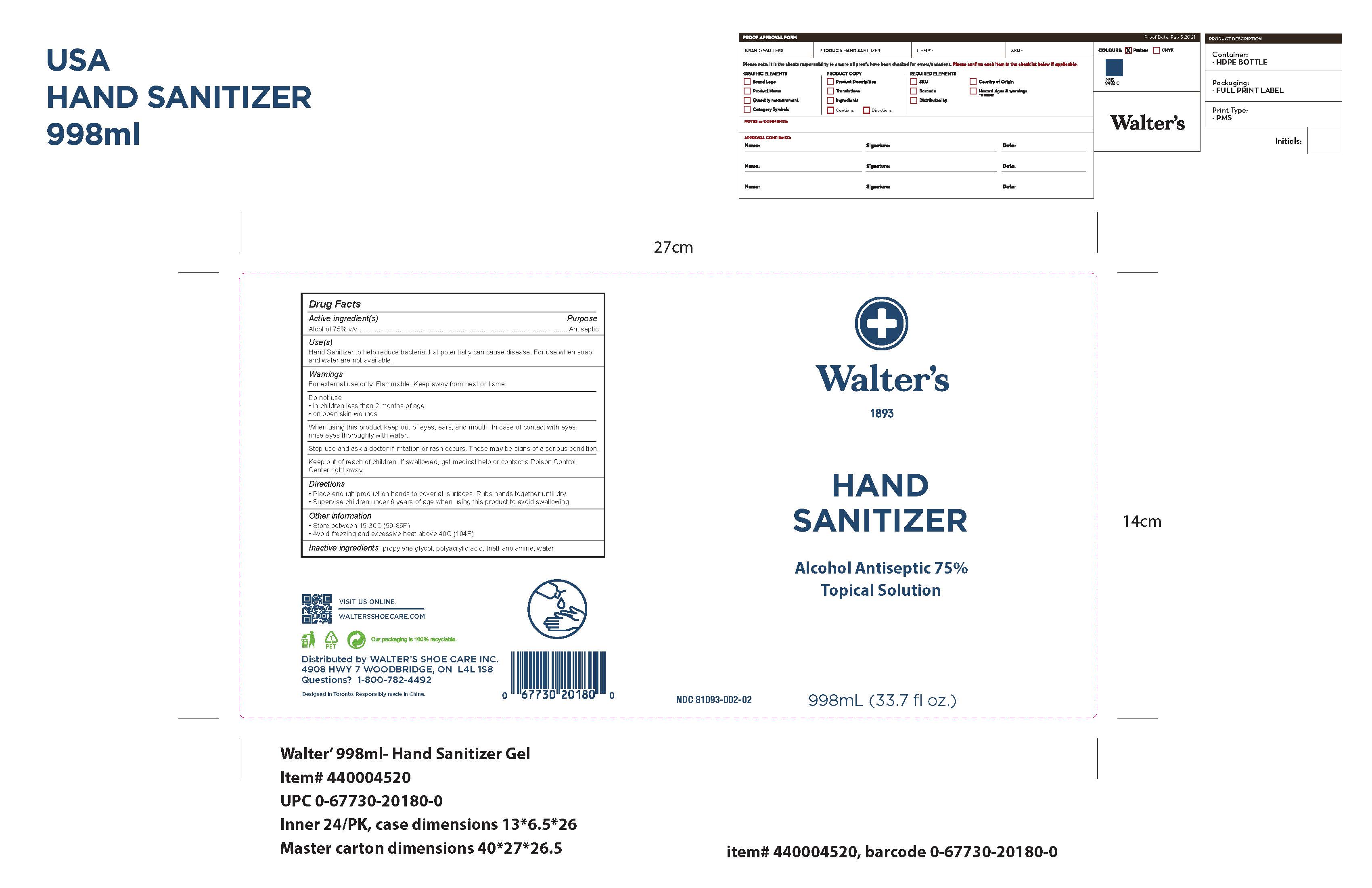 DRUG LABEL: Hand Sanitizer
NDC: 81093-002 | Form: GEL
Manufacturer: Zhongshan Biaoqi Houseware Co., LTD
Category: otc | Type: HUMAN OTC DRUG LABEL
Date: 20210217

ACTIVE INGREDIENTS: ALCOHOL 75 mL/100 mL
INACTIVE INGREDIENTS: POLYACRYLIC ACID (250000 MW) 0.3 mL/100 mL; PROPYLENE GLYCOL 2.5 mL/100 mL; TROLAMINE 0.3 mL/100 mL; WATER 21.9 mL/100 mL

Walter's 1893 Hand Sanitizer Alcohol Antiseptic 75% Topical Solution

This is a hand sanitizer manufactured using the following United States Pharmacopoeia (USP) grade ingredients in the preparation of the product (percentage in final product formulation):

1. Alcohol (ethanol) (USP or Food Chemical Codex (FCC) grade) (75%, volume/volume (v/v)) in an aqueous solution denatured according to Alcohol and Tobacco Tax and Trade Bureau regulations in 27 CFR part 20.
2. Propylene glycol (2.5% v/v).
3. Polyacrylic acid (0.3% v/v).
4. Triethanolamine (0.3% v/v).
5. Sterile distilled water (21.9% v/v).

The firm does not add other active or inactive ingredients.

Purpose

Antiseptic

Use

Hand Sanitizer to help reduce bacteria that potentially can cause disease. For use when soap and water are not available.

Warnings

For external use only. Flammable. Keep away from heat or flame

Do not use

- in children less than 2 months of age
- on open skin wounds

When using this product keep out of eyes, ears, and mouth. In case of contact with eyes, rinse eyes thoroughly with water.
Stop use and ask a doctor if irritation or rash occurs. These may be signs of a serious condition.
Keep out of reach of children. If swallowed, get medical help or contact a Poison Control Center right away.

Stop use and ask a doctor if irritation or rash occurs. These may be signs of a serious condition.

Keep out of reach of children. If swallowed, get medical help or contact a Poison Control Center right away.

Directions

- Place enough product on hands to cover all surfaces. Rub hands together until dry.
- Supervise children under 6 years of age when using this product to avoid swallowing.

Other information

- Store between 15-30C (59-86F)
- Avoid freezing and excessive heat above 40C (104F)

Inactive ingredients

propylene glycol , polyacrylic acid, triethanolamine, purified water USP

Active Ingredient(s)

Alcohol 75% v/v. Purpose: Antiseptic

Package Label - Principal Display Panel

500 mL NDC: 81093-002-01

998mL NDCL 81093-002-02